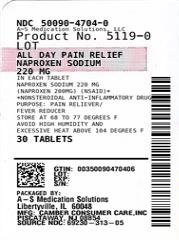 DRUG LABEL: Naproxen sodium
NDC: 50090-4704 | Form: TABLET
Manufacturer: A-S Medication Solutions
Category: otc | Type: Human OTC Drug Label
Date: 20210209

ACTIVE INGREDIENTS: NAPROXEN SODIUM 220 mg/1 1
INACTIVE INGREDIENTS: FD&C BLUE NO. 2; HYPROMELLOSE, UNSPECIFIED; MAGNESIUM STEARATE; MICROCRYSTALLINE CELLULOSE; POLYETHYLENE GLYCOL, UNSPECIFIED; POLYSORBATE 80; POVIDONE, UNSPECIFIED; SODIUM STARCH GLYCOLATE TYPE A POTATO; STARCH, CORN; TALC; TITANIUM DIOXIDE

Naproxen Sodium Tablets, USP 220 mg (NSAID)

ACTIVE INGREDIENT(S)

(in each tablet)
Naproxen sodium 220mg
(naproxen 200mg) (NSAID)*
*nonsteroidal anti-inflammatory drug

PURPOSE

Pain reliever/Fever reducer

USE(S)

■ temporarily relieves minor aches and pains due to:
■ minor pain of arthritis ■ muscular aches
■ backache ■ menstrual cramps
■ headache ■ toothache
■ the common cold
■ temporarily reduces fever

WARNINGS

Allergy alert: Naproxen sodium may cause a severe
allergic reaction, especially in people allergic to aspirin.
Symptoms may include:
■ hives ■ facial swelling
■ asthma (wheezing) ■ shock ■ skin reddening
■ rash ■ blisters
If an allergic reaction occurs, stop use and seek medical
help right away.
Stomach bleeding warning: This product contains an
NSAID, which may cause severe stomach bleeding.
The chance is higher if you:
■ are age 60 or older
■ have had stomach ulcers or bleeding problems
■ take a blood thinning (anticoagulant) or steroid drug
■ take other drugs containing prescription or
nonprescription NSAIDs (aspirin, ibuprofen, naproxen,
or others)
■ have 3 or more alcoholic drinks every day while using
this product
■ take more or for a longer time than directed.
Heart attack and stroke warning: NSAIDs, except aspirin,
increase the risk of heart attack, heart failure and stroke.
These can be fatal. The risk is higher if you use more than
directed or for longer than directed.

DO NOT USE

■ if you have ever had an allergic reaction to
any other pain reliever/fever reducer
■ right before or after heart surgery

ASK A DOCTOR BEFORE USE IF

■ the stomach bleeding warning applies to you
■ you have a history of stomach problems, such as
heartburn
■ you have high blood pressure, heart disease, liver
cirrhosis, kidney disease, asthma, or had a stroke
■ you are taking a diuretic
■ you have problems or serious side effects from
taking pain relievers or fever reducers

ASK A DOCTOR OR PHARMACIST BEFORE USE IF

■ under a doctor's care for any serious condition
■ taking any other drug

WHEN USING THIS PRODUCT

■ take with food or milk if stomach upset occurs

STOP USE AND ASK DOCTOR IF

■ you experience any of the
following signs of stomach bleeding:
■ feel faint
■ vomit blood ■ have bloody or black stools
■ have stomach pain that does not get better
■ you have symptoms of heart problems or stroke:
■ chest pain ■ trouble breathing
■ weakness in one part or side of body
■ slurred speech ■ leg swelling
■ pain gets worse or lasts more than 10 days
■ fever gets worse or lasts more than 3 days
■ you have difficulty swallowing
■ it feels like the pill is stuck in your throat
■ redness of swelling is present in the painful area
■ any new symptoms appear
You may report side effects to FDA at 1-800-FDA-1088

PREGNANCY/BREASTFEEDING

If pregnant or breast-feeding, ask a health professional before use. It is especially important not to use naproxen sodium during the last 3 months of pregnancy unless definitely directed to do so by a doctor because it may cause problems in the unborn child or complications during delivery.

KEEP OUT OF REACH OF CHILDREN

In case of overdose, get medical help or contact a Poison Control Center right away.

DIRECTIONS

■ do not take more than directed
■ the smallest effective dose should be used
■ drink a full glass of water with each dose

Adults and children 12 years and over | ■ take 1 tablet every 8 to 12 hours while symptoms last ■ for the first dose you may take 2 tablets within the first hour ■ do not exceed 2 tablets in any 8- to 12-hour period ■ do not exceed 3 tablets in a 24-hr period
Children under 12 years | ■ ask a doctor

OTHER INFORMATION

■ each tablet contains: sodium 20mg
■ store at 20 to 25^0C (68 to 77^0F). Avoid high
humidity and excessive heat above 40^0C (104^0F).

INACTIVE INGREDIENTS

FD&C blue #2 lake, hypromellose, magnesium stearate, microcrystalline cellulose, polyethylene glycol, polysorbate 80, povidone, sodium starch glycolate, starch, talc, titanium dioxide

QUESTIONS OR COMMENTS

888-588-1418 (MON - FRI 9 AM to 5 PM EST)
Distributed By: Camber Consumer Care, Inc.
Piscataway, NJ 08854, USA